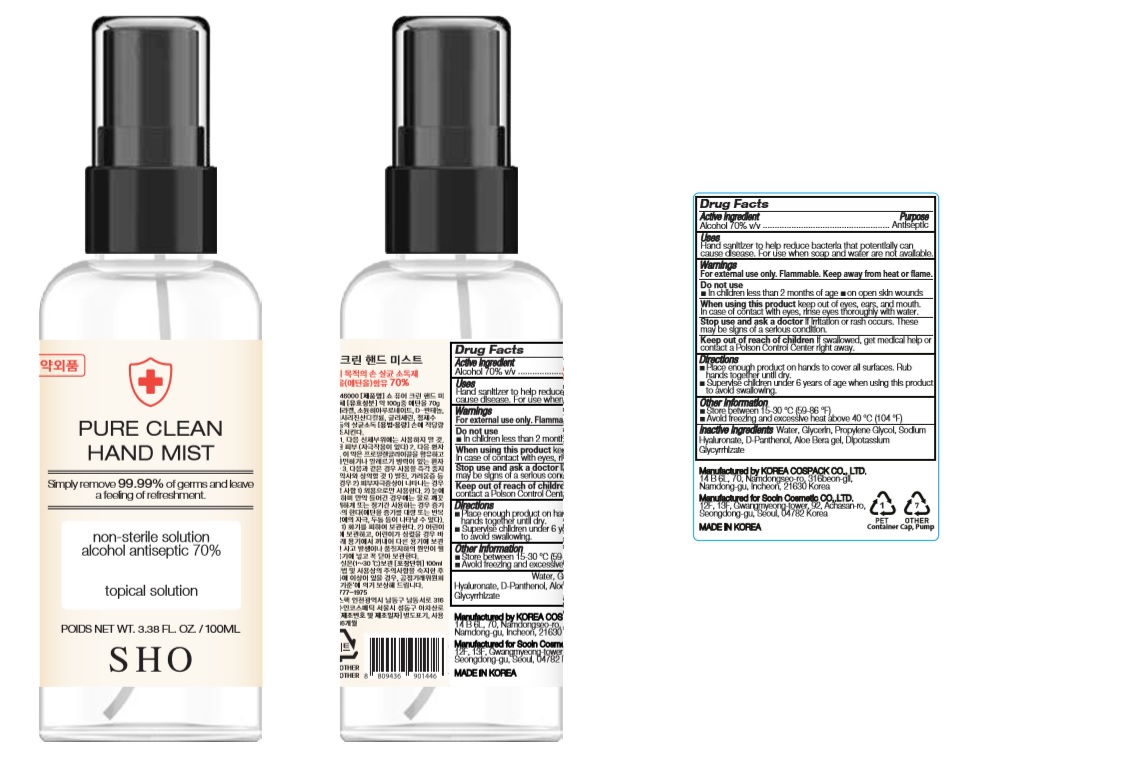 DRUG LABEL: PURE CLEAN HAND MIST
NDC: 74064-2170 | Form: LIQUID
Manufacturer: KOREA COSPACK CO.,LTD.
Category: otc | Type: HUMAN OTC DRUG LABEL
Date: 20200402

ACTIVE INGREDIENTS: ALCOHOL 70 mL/100 mL
INACTIVE INGREDIENTS: PROPYLENE GLYCOL; GLYCERIN; GLYCYRRHIZINATE DIPOTASSIUM; WATER; DEXPANTHENOL; HYALURONATE SODIUM; ALOE VERA LEAF

PURE CLEAN HAND MIST 100 ml : 74064-2170